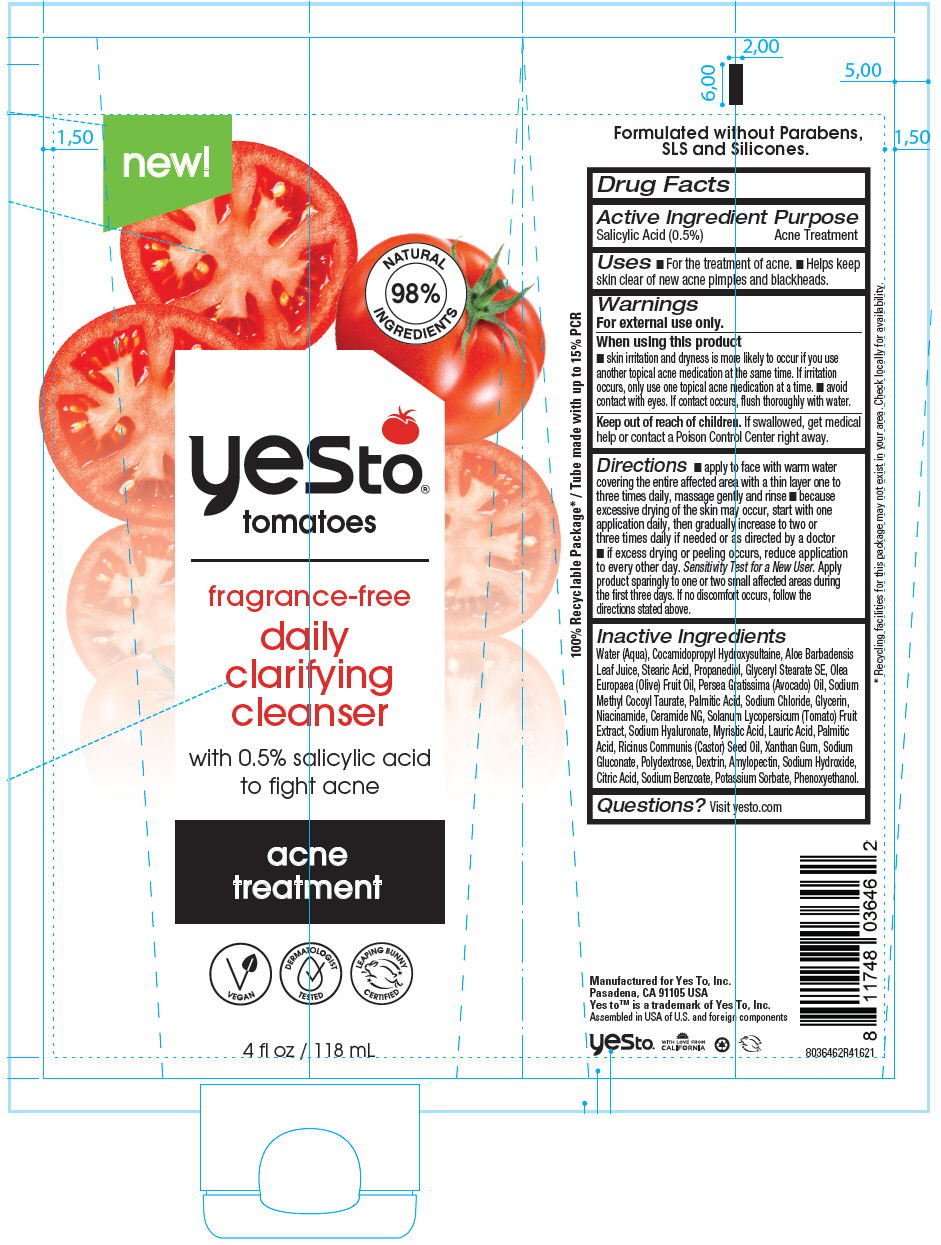 DRUG LABEL: Yes To Tomatoes Fragrance-Free Daily Clarifying Cleanser
NDC: 69840-029 | Form: CREAM
Manufacturer: Yes To, Inc.
Category: otc | Type: HUMAN OTC DRUG LABEL
Date: 20220126

ACTIVE INGREDIENTS: Salicylic Acid 5 mg/1 mL
INACTIVE INGREDIENTS: Water; Sodium Gluconate; Sodium Benzoate; Potassium Sorbate; CITRIC ACID MONOHYDRATE; ALOE VERA LEAF; Xanthan Gum; Sodium Methyl Cocoyl Taurate; TOMATO; Phenoxyethanol; Cocamidopropyl Hydroxysultaine; Sodium Chloride; Sodium Hydroxide; HYALURONATE SODIUM; Glycerin; Propanediol; Niacinamide; ICODEXTRIN; Polydextrose; AMYLOPECTIN, CORN; AVOCADO OIL; OLIVE OIL; Stearic Acid; Myristic Acid; Lauric Acid; Palmitic Acid; Glyceryl Stearate SE; CASTOR OIL; Ceramide NG

Yes To® Tomatoes Fragrance-Free Daily Clarifying Cleanser

Drug Facts

Active Ingredient

Salicylic Acid (0.5%)

Purpose

Acne Treatment

Uses

- For the treatment of acne.
- Helps keep skin clear of new acne pimples and blackheads.

Warnings

For external use only.

When using this product

- skin irritation and dryness is more likely to occur if you use another topical acne medication at the same time. If irritation occurs, only use one topical acne medication at a time.
- avoid contact with eyes. If contact occurs, flush thoroughly with water.

Keep out of reach of children. If swallowed, get medical help or contact a Poison Control Center right away.

Directions

- apply to face with warm water covering the entire affected area with a thin layer one to three times daily, massage gently and rinse
- because excessive drying of the skin may occur, start with one application daily, then gradually increase to two or three times daily if needed or as directed by a doctor
- if excess drying or peeling occurs, reduce application to every other day. Sensitivity Test for a New User. Apply product sparingly to one or two small affected areas during the first three days. If no discomfort occurs, follow the directions stated above.

Inactive Ingredients

Water (Aqua), Cocamidopropyl Hydroxysultaine, Aloe Barbadensis Leaf Juice, Stearic Acid, Propanediol, Glyceryl Stearate SE, Olea Europaea (Olive) Fruit Oil, Persea Gratissima (Avocado) Oil, Sodium Methyl Cocoyl Taurate, Palmitic Acid, Sodium Chloride, Glycerin, Niacinamide, Ceramide NG, Solanum Lycopersicum (Tomato) Fruit Extract, Sodium Hyaluronate, Myristic Acid, Lauric Acid, Palmitic Acid, Ricinus Communis (Castor) Seed Oil, Xanthan Gum, Sodium Gluconate, Polydextrose, Dextrin, Amylopectin, Sodium Hydroxide, Citric Acid, Sodium Benzoate, Potassium Sorbate, Phenoxyethanol.

Questions?

Visit yesto.com

PRINCIPAL DISPLAY PANEL - 118 mL Tube Label

new!

98%
NATURAL
INGREDIENTS

yesto®
tomatoes

fragrance-free

daily
clarifying
cleanser

with 0.5% salicylic acid
to fight acne

acne
treatment

VEGAN

DERMATOLOGIST
TESTED

LEAPING BUNNY
CERTIFIED

4 fl oz / 118 mL